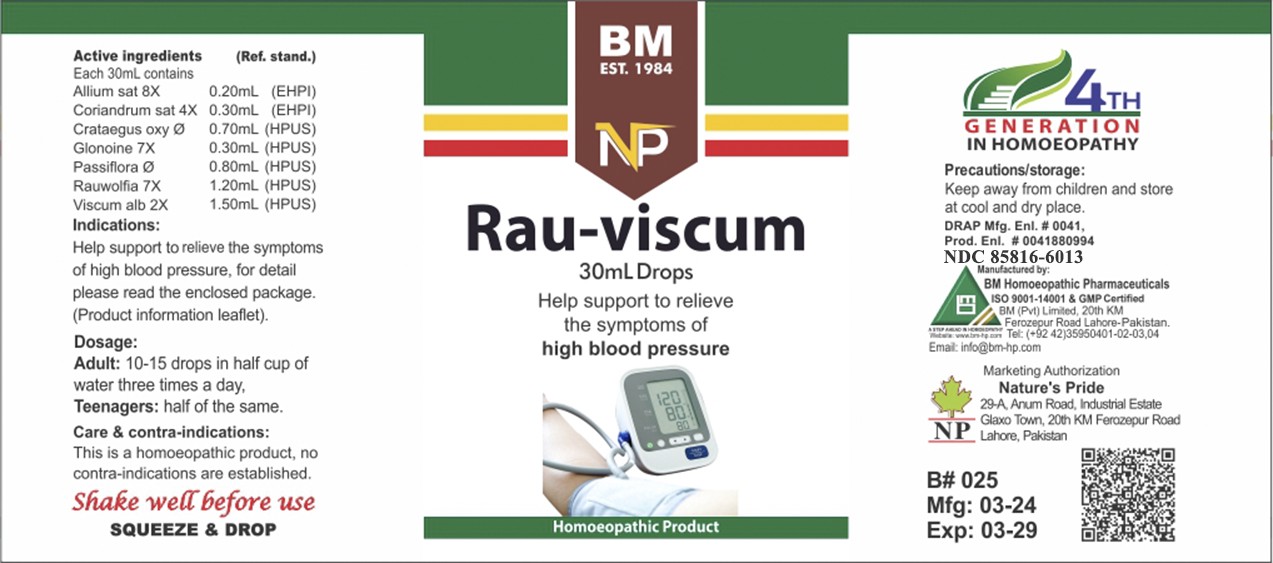 DRUG LABEL: RAU VISCUM
NDC: 85816-6013 | Form: LIQUID
Manufacturer: BM Private Limited
Category: homeopathic | Type: HUMAN OTC DRUG LABEL
Date: 20250731

ACTIVE INGREDIENTS: CRATAEGUS LAEVIGATA WHOLE 1 [hp_X]/1 mL; VISCUM ALBUM FRUITING TOP 2 [hp_X]/1 mL; CILANTRO 4 [hp_X]/1 mL; PASSIFLORA INCARNATA FLOWERING TOP 1 [hp_X]/1 mL; NITROGLYCERIN 7 [hp_X]/1 mL; RAUWOLFIA SERPENTINA 7 [hp_X]/1 mL; GARLIC 8 [hp_X]/1 mL
INACTIVE INGREDIENTS: ALCOHOL 0.96 mL/1 mL

BM HOMEOPATHIC LIQUID RAU VISCUM

Dosage:
Adult:10-15 drops in half cup of water three times a day
Teenagers: half of the same

ACTIVE INGREDIENT

allium sat, coriandrum sat, crataegus oxy, glonoine, passiflora, rowolfia, viscum alb

INACTIVE INGREDIENT

Alcohol

INDICATIONS AND USAGE

Help support to relieve the symptoms of high blood pressure, for detail please read the enclosed package.
(Product information leaflet).

PURPOSE

Help support to relieve the symptoms of high blood pressure, for detail please read the enclosed package.
(Product information leaflet).

CONTRAINDICATIONS

Care & contra-indications:
This is a homoeopathic remedy, no contra-indications are established.

WARNINGS

Precautions/storage:
Keep away from children and store at cool and dry place.

KEEP OUT OF REACH OF CHILDREN

Precautions/storage:
Keep away from children and store at cool and dry place.